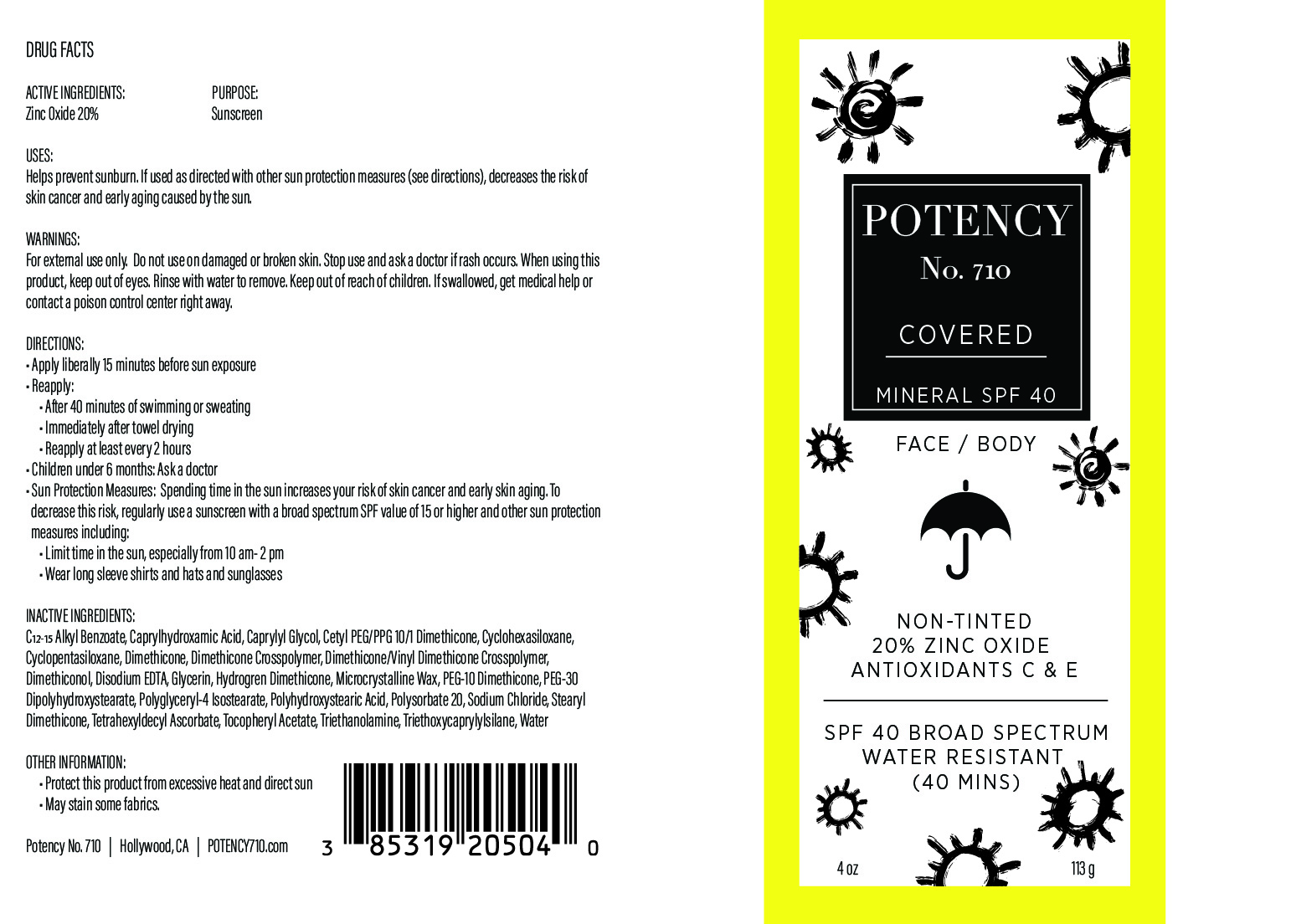 DRUG LABEL: COVERED
NDC: 85319-205 | Form: CREAM
Manufacturer: Potency No. 710 LLC
Category: otc | Type: HUMAN OTC DRUG LABEL
Date: 20251210

ACTIVE INGREDIENTS: ZINC OXIDE 200 mg/1 g
INACTIVE INGREDIENTS: CAPRYLYL GLYCOL; TRIETHOXYCAPRYLYLSILANE; CYCLOHEXASILOXANE; DIMETHICONE; HYDROGEN DIMETHICONE (20 CST); TETRAHEXYLDECYL ASCORBATE; PEG-10 DIMETHICONE (600 CST); POLYSORBATE 20; SODIUM CHLORIDE; STEARYL DIMETHICONE (400 MPA.S AT 50C); POLYHYDROXYSTEARIC ACID (2300 MW); WATER; MICROCRYSTALLINE WAX; TRIETHANOLAMINE; DIMETHICONE/VINYL DIMETHICONE CROSSPOLYMER (SOFT PARTICLE); POLYGLYCERYL-4 ISOSTEARATE; ALPHA-TOCOPHEROL ACETATE; CAPRYLHYDROXAMIC ACID; CYCLOPENTASILOXANE; C12-15 ALKYL BENZOATE; GLYCERIN; DIMETHICONOL (2000 CST); PEG-30 DIPOLYHYDROXYSTEARATE; DIMETHICONE CROSSPOLYMER; CETYL PEG/PPG-10/1 DIMETHICONE (HLB 4); EDETATE DISODIUM ANHYDROUS

Active Ingredients:

Zinc Oxide 20%

Purpose:

Sunscreen

Uses:

Helps prevents sunburn. If used as directed with other sun protection measures (see Directions), decreases the risk of skin cancer and early skin aging caused by the sun.

Warnings:

For external use only. Do not use on damaged or broken skin. Stop use and ask a doctor if rash occurs. When using this product, keep out of eyes. Rinse with water to remove. Keep out of the reach of children. If swallowed, get medical help or contact a poison control center right away.

Warnings:

Keep out of reach of children

Directions:

• Apply liberally 15 minutes before sun exposure. • Reapply: • After 80 minutes of swimming or sweating • Immediately after towel drying • At least every 2 hours • Children under 6 months: Ask a doctor • Sun Protection Measures: Spending time in the sun increases your risk of skin cancer and early skin aging. To decrease this risk, regularly use a sunscreen with a Broad Spectrum SPF value of 15 or higher and other sun protection measures including: •Limit time in the sun, especially from 10 am-2 pm •Wear long-sleeved shirts, pants, hats, and sunglasses

Inactive Ingredients:

C12-15 Alkyl Benzoate, Caprylhydroxamic Acid, Caprylyl Glycol, Cetyl PEG/PPG-10/1 Dimethicone, Cyclohexasiloxane, Cyclopentasiloxane, Dimethicone, Dimethicone Crosspolymer, Dimethicone/Vinyl Dimethicone Crosspolymer, Dimethiconol, Disodium EDTA, Glycerin, Hydrogen Dimethicone, Microcrystalline Wax, PEG-10 Dimethicone, PEG-30 Dipolyhydroxystearate, Polyglyceryl-4 Isostearate, Polyhydroxystearic Acid, Polysorbate 20, Sodium Chloride, Stearyl Dimethicone, Tetrahexyldecyl Ascorbate, Tocopheryl Acetate, Triethanolamine, Triethoxycaprylylsilane, Water

Other Information:

- Protect this product from excessive heat and direct sun.
- May stain some fabrics.